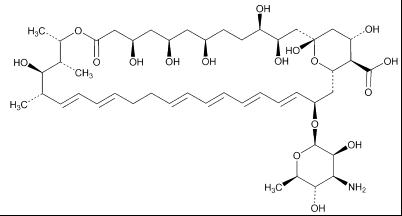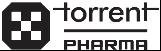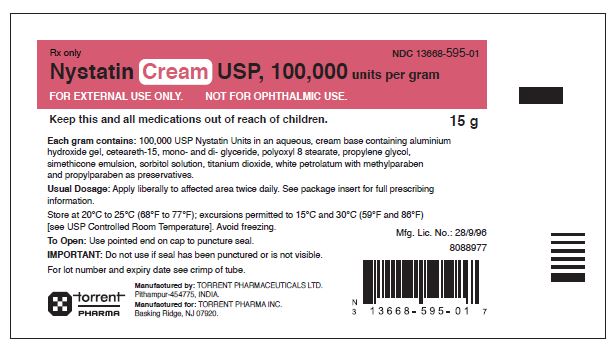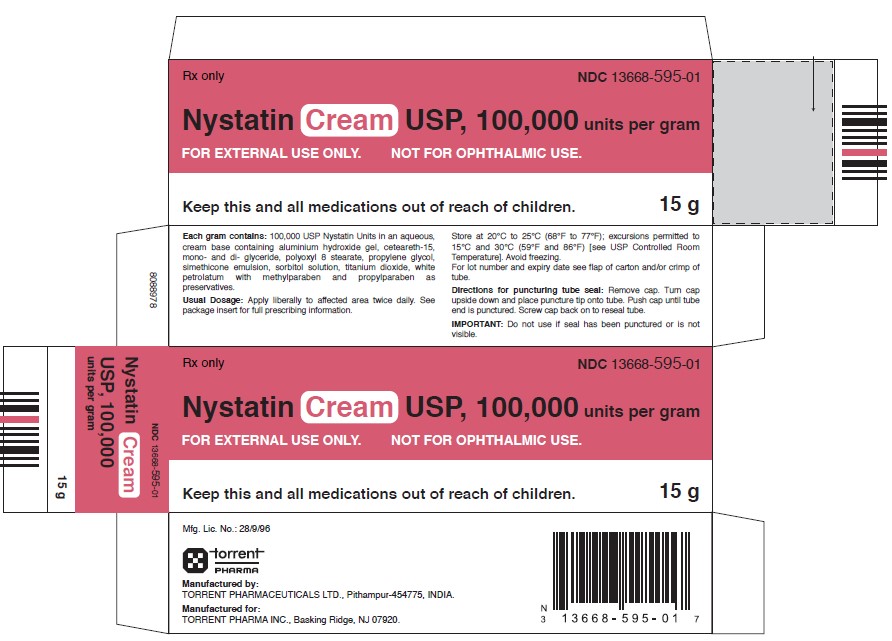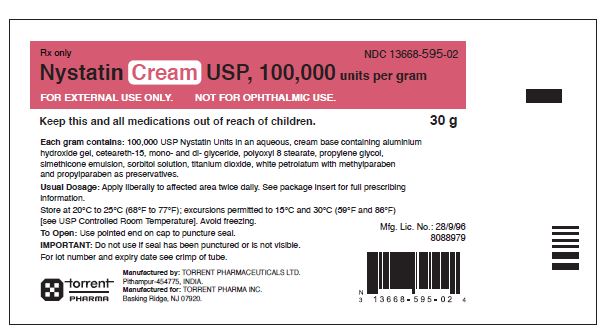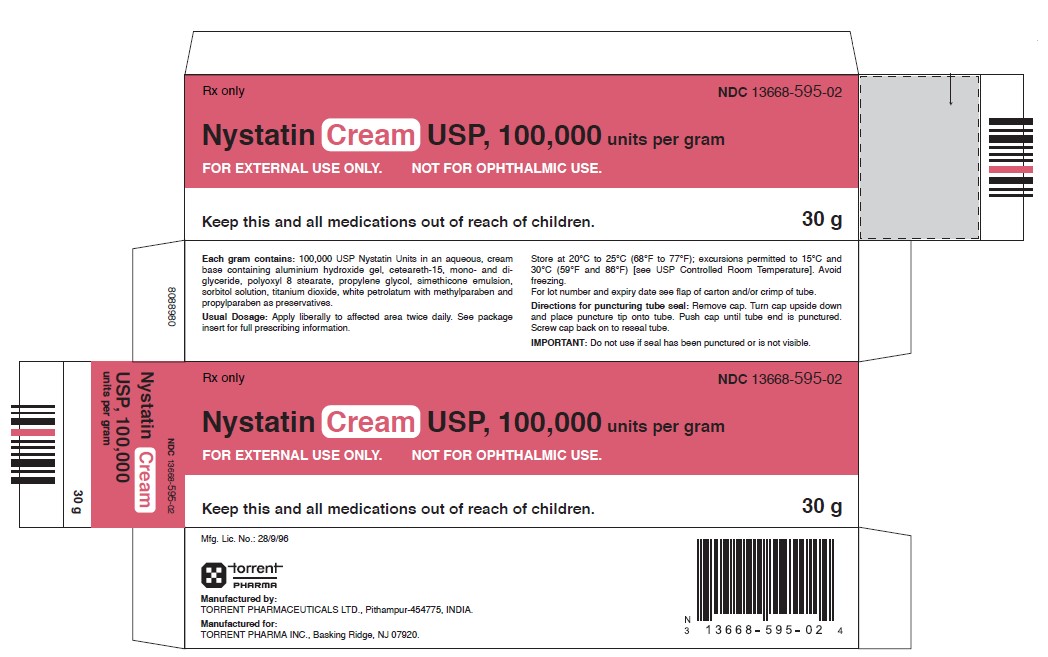 DRUG LABEL: Nystatin
NDC: 67296-1519 | Form: CREAM
Manufacturer: RedPharm Drug, Inc
Category: prescription | Type: HUMAN PRESCRIPTION DRUG LABEL
Date: 20260124

ACTIVE INGREDIENTS: NYSTATIN 100000 U/1 g
INACTIVE INGREDIENTS: PROPYLENE GLYCOL; PROPYLPARABEN; SORBITOL; TITANIUM DIOXIDE; ALUMINUM HYDROXIDE; CETEARETH-15; DIMETHICONE; GLYCERYL MONOSTEARATE; METHYLPARABEN; PETROLATUM; POLYOXYL 8 STEARATE

Nystatin Cream USP, 100,000 units per gram
FOR TOPICAL USE ONLY. NOT FOR OPHTHALMIC USE

DESCRIPTION

Nystatin is a polyene antifungal antibiotic obtained from Streptomyces nursei.

Structural formula:

Molecular formula | : | C47H75NO17
Molecular weight | : | 926.09 g/mol

Nystatin cream is for dermatologic use.

Nystatin cream, USP for topical use, contains 100,000 USP nystatin units per gram. Inactive ingredients: aluminium hydroxide gel, ceteareth-15, mono- and di- glyceride, polyoxyl 8 stearate, propylene glycol, simethicone emulsion, sorbitol solution, titanium dioxide, white petrolatum, methylparaben and propylparaben.

CLINICAL PHARMACOLOGY

Pharmacokinetics

Nystatin is not absorbed from intact skin or mucous membrane.

Microbiology

Nystatin is an antibiotic which is both fungistatic and fungicidal in vitro against a wide variety of yeasts and yeast-like fungi, including Candida albicans, C. parapsilosis, C. tropicalis, C. guilliermondi, C. pseudotropicalis, C. krusei, Torulopsis glabrata, Tricophyton rubrum, T. mentagrophytes. Nystatin acts by binding to sterols in the cell membrane of susceptible species resulting in a change in membrane permeability and the subsequent leakage of intracellular components. On repeated subculturing with increasing levels of nystatin, Candida albicans does not develop resistance to nystatin. Generally, resistance to nystatin does not develop during therapy. However, other species of Candida (C. tropicalis, C. guilliermondi, C. krusei, and C. stellatoides) become quite resistant on treatment with nystatin and simultaneously become cross resistant to amphotericin as well. This resistance is lost when the antibiotic is removed. Nystatin exhibits no appreciable activity against bacteria, protozoa, or viruses.

INDICATIONS AND USAGE

Nystatin cream is indicated in the treatment of cutaneous or mucocutaneous mycotic infections caused by Candida albicans and other susceptible Candida species.

This cream is not indicated for systemic, oral, intravaginal or ophthalmic use.

CONTRAINDICATIONS

Nystatin cream is contraindicated in patients with a history of hypersensitivity to any of their components.

PRECAUTIONS

General

Nystatin cream should not be used for the treatment of systemic, oral, intravaginal or ophthalmic infections.

If irritation or sensitization develops, treatment should be discontinued and appropriate measures taken as indicated. It is recommended that KOH smears, cultures, or other diagnostic methods be used to confirm the diagnosis of cutaneous or mucocutaneous candidiasis and to rule out infection caused by other pathogens.

INFORMATION FOR PATIENTS

Patients using these medications should receive the following information and instructions:

1. The patient should be instructed to use these medications as directed (including the replacement of missed doses). This medication is not for any disorder other than that for which it is prescribed.

2. Even if symptomatic relief occurs within the first few days of treatment, the patient should be advised not to interrupt or discontinue therapy until the prescribed course of treatment is completed.

3. If symptoms of irritation develop, the patient should be advised to notify the physician promptly.

Laboratory Tests

If there is a lack of therapeutic response, KOH smears, cultures, or other diagnostic methods should be repeated.

Carcinogenesis, Mutagenesis, Impairment of Fertility

No long-term animal studies have been performed to evaluate the carcinogenic potential of nystatin. No studies have been performed to determine the mutagenicity of nystatin or its effects on male or female fertility.

Pregnancy

Teratogenic Effects

Category C.

Animal reproduction studies have not been conducted with any nystatin cream. It also is not known whether this cream can cause fetal harm when used by a pregnant woman or can affect reproductive capacity. Nystatin cream should be prescribed for a pregnant woman only if the potential benefit to the mother outweighs the potential risk to the fetus.

Nursing Mothers

It is not known whether nystatin is excreted in human milk. Caution should be exercised when nystatin is prescribed for a nursing woman.

Pediatric Use

Safety and effectiveness have been established in the pediatric population from birth to 16 years.

(See DOSAGE AND ADMINISTRATION)

Geriatric Use

Clinical studies with nystatin cream did not include sufficient numbers of subjects aged 65 years and older to determine whether they respond differently than younger subjects. Other reported clinical experience has not identified differences in responses between elderly and younger patients, but greater sensitivity of some older individuals cannot be ruled out.

ADVERSE REACTIONS

The frequency of adverse events reported in patients using nystatin cream is less than 0.1%. The more common events that were reported include allergic reactions, burning, itching, rash, eczema, and pain on application.

(See PRECAUTIONS: General.)

DOSAGE AND ADMINISTRATION

Adults and Pediatric Patients (Neonates and Older)

Apply liberally to affected areas twice daily or as indicated until health is complete.

HOW SUPPLIED

Nystatin Cream, USP, 100,000 units per gram is a yellow to light green color cream available as follows:

NDC 13668-595-01 15 g tube

NDC 13668-595-02 30 g tube

STORAGE AND HANDLING

Store at 20°C to 25°C (68°F to 77°F); excursions permitted between 15°C and 30°C (59°F and 86°F) [see USP Controlled Room Temperature]. Avoid freezing.

Manufactured by:

TORRENT PHARMACEUTICALS LTD., Pithampur-454775, INDIA .

Manufactured for:

TORRENT PHARMA INC., Basking Ridge, NJ 07920

8088981 August 2022